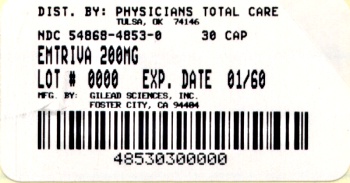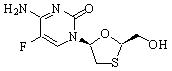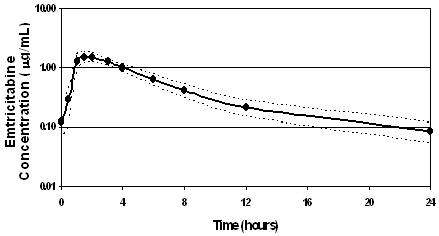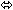 DRUG LABEL: Emtriva
NDC: 54868-4853 | Form: CAPSULE
Manufacturer: Physicians Total Care, Inc.
Category: prescription | Type: HUMAN PRESCRIPTION DRUG LABEL
Date: 20120216

ACTIVE INGREDIENTS: emtricitabine 200 mg/1 1
INACTIVE INGREDIENTS: cellulose, microcrystalline; crospovidone; povidone; magnesium stearate; water; FD&C BLUE NO. 2; titanium dioxide; gelatin

HIGHLIGHTS OF PRESCRIBING INFORMATION

These highlights do not include all the information needed to use EMTRIVA safely and effectively. See full prescribing information for EMTRIVA.
EMTRIVA (emtricitabine) capsule for oral use
EMTRIVA® (emtricitabine) solution for oral use
Initial U.S. Approval: 2003

WARNINGS: LACTIC ACIDOSIS/SEVERE HEPATOMEGALY WITH STEATOSIS and POST TREATMENT EXACERBATION OF HEPATITIS B

See full prescribing information for complete boxed warning.

- Lactic acidosis and severe hepatomegaly with steatosis, including fatal cases, have been reported with the use of nucleoside analogs. (5.1)
- Emtriva is not approved for the treatment of chronic Hepatitis B virus (HBV) infection. Severe acute exacerbations of Hepatitis B have been reported in patients who have discontinued EMTRIVA. Hepatic function should be monitored closely in patients coinfected with HIV-1 and HBV. If appropriate, initiation of anti-Hepatitis B therapy may be warranted. (5.2)

RECENT MAJOR CHANGES

Indications and Usage (1) | 11/2011
Warnings and Precautions
Coadministration with Other Products (5.3) | 11/2011
Immune Reconstitution Syndrome (5.6) | 11/2011

1 INDICATIONS AND USAGE

EMTRIVA, a nucleoside analog HIV-1 reverse transcriptase inhibitor, is indicated in combination with other antiretroviral agents for the treatment of HIV-1 infection. (1)

2 DOSAGE AND ADMINISTRATION

- EMTRIVA may be taken without regard to food. (2.1)
- Adult Patients (18 years of age and older) (2.2):
  - EMTRIVA capsules: one 200 mg capsule administered once daily orally.
  - EMTRIVA oral solution: 240 mg (24 mL) administered once daily orally.
- Pediatric Patients (0–3 months of age) (2.3):
  - EMTRIVA oral solution: 3 mg/kg administered once daily orally.
- Pediatric Patients (3 months through 17 years) (2.4):
  - EMTRIVA oral solution: 6 mg/kg up to a maximum of 240 mg (24 mL) administered once daily orally.
  - EMTRIVA capsules: for children weighing more than 33 kg who can swallow an intact capsule, one 200 mg capsule administered once daily orally.
- Dose interval adjustment in adult patients with renal impairment (2.5):

 | Creatinine Clearance (mL/min)
Formulation | ≥50 mL/min | 30–49 mL/min | 15–29 mL/min | <15 mL/min or on hemodialysis [Hemodialysis Patients: If dosing on day of dialysis, give dose after dialysis.]
Capsule (200 mg) | 200 mg every 24 hours | 200 mg every 48 hours | 200 mg every 72 hours | 200 mg every 96 hours
Oral Solution (10 mg/mL) | 240 mg every 24 hours (24 mL) | 120 mg every 24 hours (12 mL) | 80 mg every 24 hours (8 mL) | 60 mg every 24 hours (6 mL)

3 DOSAGE FORMS AND STRENGTHS

- Capsules: 200 mg (3)
- Oral solution: 10 mg per mL (3)

4 CONTRAINDICATIONS

EMTRIVA is contraindicated in patients with previously demonstrated hypersensitivity to any of the components of the products. (4)

5 WARNINGS AND PRECAUTIONS

- Products with same active ingredient: Do not use with other emtricitabine-containing products (e.g., ATRIPLA, COMPLERA and TRUVADA). (5.3)
- Redistribution/accumulation of body fat: Observed in patients receiving antiretroviral therapy. (5.5)
- Immune reconstitution syndrome: May necessitate further evaluation and treatment. (5.6)

6 ADVERSE REACTIONS

Most common adverse reactions (incidence ≥10%) are headache, diarrhea, nausea, fatigue, dizziness, depression, insomnia, abnormal dreams, rash, abdominal pain, asthenia, increased cough, and rhinitis. Skin hyperpigmentation was very common (≥10%) in pediatric patients. (6)

To report SUSPECTED ADVERSE REACTIONS, contact Gilead Sciences, Inc. at 1-800-GILEAD-5 or FDA at 1-800-FDA-1088 or www.fda.gov/medwatch

8 USE IN SPECIFIC POPULATIONS

- Nursing mothers: Women infected with HIV should be instructed not to breast feed. (8.3)
- Pediatrics: Dose adjustment based on age and weight. (2.3, 2.4, 12.3)

FULL PRESCRIBING INFORMATION

WARNINGS: LACTIC ACIDOSIS/SEVERE HEPATOMEGALY WITH STEATOSIS and POST TREATMENT EXACERBATION OF HEPATITIS B

Lactic acidosis and severe hepatomegaly with steatosis, including fatal cases, have been reported with the use of nucleoside analogs alone or in combination with other antiretrovirals [See Warnings and Precautions (5.1)].

EMTRIVA is not approved for the treatment of chronic hepatitis B virus (HBV) infection and the safety and efficacy of EMTRIVA have not been established in patients coinfected with HBV and HIV-1. Severe acute exacerbations of hepatitis B have been reported in patients who have discontinued EMTRIVA. Hepatic function should be monitored closely with both clinical and laboratory follow-up for at least several months in patients who are coinfected with HIV-1 and HBV and discontinue EMTRIVA. If appropriate, initiation of anti-hepatitis B therapy may be warranted [See Warnings and Precautions (5.2)].

1 INDICATIONS AND USAGE

EMTRIVA® is indicated in combination with other antiretroviral agents for the treatment of HIV-1 infection.

Additional important information regarding the use of EMTRIVA for the treatment of HIV-1 Infection:

- EMTRIVA should not be coadministered with ATRIPLA®, COMPLERA™, TRUVADA®, or lamivudine-containing products [See Warnings and Precautions (5.3)].
- In treatment-experienced patients, the use of EMTRIVA should be guided by laboratory testing and treatment history [See Clinical Pharmacology (12.4)].

2 DOSAGE AND ADMINISTRATION

2.1 Recommended Dose

EMTRIVA may be taken without regard to food.

2.2 Adult Patients (18 years of age and older)

- EMTRIVA capsules: one 200 mg capsule administered once daily orally.
- EMTRIVA oral solution: 240 mg (24 mL) administered once daily orally.

2.3 Pediatric Patients (0–3 months of age)

- EMTRIVA oral solution: 3 mg/kg administered once daily orally.

2.4 Pediatric Patients (3 months through 17 years)

- EMTRIVA oral solution: 6 mg/kg up to a maximum of 240 mg (24 mL) administered once daily orally.
- EMTRIVA capsules: for children weighing more than 33 kg who can swallow an intact capsule, one 200 mg capsule administered once daily orally.

2.5 Dose Adjustment in Adult Patients with Renal Impairment

Significantly increased drug exposures were seen when EMTRIVA was administered to patients with renal impairment [See Clinical Pharmacology (12.3)]. Therefore, the dosing interval or dose of EMTRIVA should be adjusted in patients with baseline creatinine clearance <50 mL/min using the following guidelines (see Table 1). The safety and effectiveness of these dose adjustment guidelines have not been clinically evaluated. Therefore, clinical response to treatment and renal function should be closely monitored in these patients.

Table 1 Dose Adjustment in Adult Patients with Renal Impairment
 | Creatinine Clearance (mL/min)
Formulation | ≥50 mL/min | 30–49 mL/min | 15–29 mL/min | <15 mL/min or on hemodialysis [Hemodialysis Patients: If dosing on day of dialysis, give dose after dialysis]
Capsule (200 mg) | 200 mg every 24 hours | 200 mg every 48 hours | 200 mg every 72 hours | 200 mg every 96 hours
Oral Solution (10 mg/mL) | 240 mg every 24 hours (24 mL) | 120 mg every 24 hours (12 mL) | 80 mg every 24 hours (8 mL) | 60 mg every 24 hours (6 mL)

Although there are insufficient data to recommend a specific dose adjustment of EMTRIVA in pediatric patients with renal impairment, a reduction in the dose and/or an increase in the dosing interval similar to adjustments for adults should be considered.

3 DOSAGE FORMS AND STRENGTHS

EMTRIVA is available as capsules and oral solution.

EMTRIVA capsules, containing 200 mg of emtricitabine, are size 1 hard gelatin capsules with a blue cap and white body, printed with "200 mg" in black on the cap and "GILEAD" and the corporate logo in black on the body.

EMTRIVA oral solution is a clear, orange to dark orange liquid containing 10 mg of emtricitabine per mL.

4 CONTRAINDICATIONS

EMTRIVA is contraindicated in patients with previously demonstrated hypersensitivity to any of the components of the products.

5 WARNINGS AND PRECAUTIONS

5.1 Lactic Acidosis/Severe Hepatomegaly with Steatosis

Lactic acidosis and severe hepatomegaly with steatosis, including fatal cases, have been reported with the use of nucleoside analogs alone or in combination, including emtricitabine and other antiretrovirals. A majority of these cases have been in women. Obesity and prolonged nucleoside exposure may be risk factors. Particular caution should be exercised when administering nucleoside analogs to any patient with known risk factors for liver diseases; however, cases have also been reported in patients with no known risk factors. Treatment with EMTRIVA should be suspended in any patient who develops clinical or laboratory findings suggestive of lactic acidosis or pronounced hepatotoxicity (which may include hepatomegaly and steatosis even in the absence of marked transaminase elevations).

5.2 Patients Coinfected with HIV-1 and HBV

It is recommended that all patients with HIV-1 be tested for the presence of chronic Hepatitis B virus (HBV) before initiating antiretroviral therapy. EMTRIVA is not approved for the treatment of chronic HBV infection and the safety and efficacy of EMTRIVA have not been established in patients coinfected with HBV and HIV-1. Severe acute exacerbations of Hepatitis B have been reported in patients after the discontinuation of EMTRIVA. In some patients infected with HBV and treated with EMTRIVA, the exacerbations of hepatitis B were associated with liver decompensation and liver failure. Hepatic function should be monitored closely with both clinical and laboratory follow-up for at least several months in patients who are coinfected with HIV-1 and HBV and discontinue EMTRIVA. If appropriate, initiation of anti-Hepatitis B therapy may be warranted.

5.3 Coadministration with Related Products

EMTRIVA is a component of ATRIPLA (a fixed-dose combination of efavirenz, emtricitabine, and tenofovir disoproxil fumarate), COMPLERA (a fixed-dose combination of emtricitabine, rilpivirine, and tenofovir disoproxil fumarate) and TRUVADA (a fixed-dose combination of emtricitabine and tenofovir disoproxil fumarate). EMTRIVA should not be coadministered with ATRIPLA, COMPLERA, or TRUVADA. Due to similarities between emtricitabine and lamivudine, EMTRIVA should not be coadministered with other drugs containing lamivudine, including Combivir (lamivudine/zidovudine), Epivir or Epivir-HBV (lamivudine), Epzicom (abacavir sulfate/lamivudine), or Trizivir (abacavir sulfate/lamivudine/zidovudine).

5.4 New Onset or Worsening Renal Impairment

Emtricitabine is principally eliminated by the kidney. Reduction of the dosage of EMTRIVA is recommended for patients with impaired renal function [See Dosage and Administration (2.5) and Clinical Pharmacology (12.3)].

5.5 Fat Redistribution

Redistribution/accumulation of body fat including central obesity, dorsocervical fat enlargement (buffalo hump), peripheral wasting, facial wasting, breast enlargement, and "cushingoid appearance" have been observed in patients receiving antiretroviral therapy. The mechanism and long-term consequences of these events are currently unknown. A causal relationship has not been established.

5.6 Immune Reconstitution Syndrome

Immune reconstitution syndrome has been reported in patients treated with combination antiretroviral therapy, including EMTRIVA. During the initial phase of combination antiretroviral treatment, patients whose immune system responds may develop an inflammatory response to indolent or residual opportunistic infections [such as Mycobacterium avium infection, cytomegalovirus, Pneumocystis jirovecii pneumonia (PCP), or tuberculosis], which may necessitate further evaluation and treatment.

Autoimmune disorders (such as Graves' disease, polymyositis, and Guillain-Barré syndrome) have also been reported to occur in the setting of immune reconstitution, however, the time to onset is more variable, and can occur many months after initiation of treatment.

6 ADVERSE REACTIONS

The following adverse reactions are discussed in other sections of the labeling:

- Lactic acidosis/severe hepatomegaly with steatosis [See Boxed Warning, Warnings and Precautions (5.1)].
- Severe acute exacerbations of Hepatitis B [See Boxed Warning, Warnings and Precautions (5.2)].
- Immune reconstitution syndrome [See Warnings and Precautions (5.6)]

6.1 Adverse Reactions from Clinical Trials Experience

Adult Patients

More than 2,000 adult patients with HIV-1 infection have been treated with EMTRIVA alone or in combination with other antiretroviral agents for periods of 10 days to 200 weeks in clinical trials.

Because clinical trials are conducted under widely varying conditions, adverse reaction rates observed in the clinical trials of a drug cannot be directly compared to rates in the clinical trials of another drug and may not reflect the rates observed in practice.

The most common adverse reactions (incidence ≥10%, any severity) identified from any of the 3 large controlled clinical trials include headache, diarrhea nausea, fatigue, dizziness, depression, insomnia, abnormal dreams, rash, abdominal pain, asthenia, increased cough, and rhinitis.

Studies 301A and 303 - Treatment Emergent Adverse Reactions: The most common adverse reactions that occurred in patients receiving EMTRIVA with other antiretroviral agents in clinical studies 301A and 303 were headache, diarrhea, nausea, and rash, which were generally of mild to moderate severity. Approximately 1% of patients discontinued participation in the clinical studies due to these events. All adverse reactions were reported with similar frequency in EMTRIVA and control treatment groups with the exception of skin discoloration which was reported with higher frequency in the EMTRIVA treated group.

Skin discoloration, manifested by hyperpigmentation on the palms and/or soles was generally mild and asymptomatic. The mechanism and clinical significance are unknown.

A summary of EMTRIVA treatment emergent clinical adverse reactions in studies 301A and 303 is provided in Table 2.

Table 2 Selected Treatment-Emergent Adverse Reactions (All Grades, Regardless of Causality) Reported in ≥3% of EMTRIVA-Treated Patients in Either Study 301A or 303 (0–48 Weeks)
 | 303 |  | 301A
 | EMTRIVA + ZDV/d4T + NNRTI/PI (N=294) | Lamivudine + ZDV/d4T + NNRTI/PI (N=146) | EMTRIVA + didanosine + efavirenz (N=286) | Stavudine + didanosine + efavirenz (N=285)
Body as a Whole
Abdominal pain | 8% | 11% | 14% | 17%
Asthenia | 16% | 10% | 12% | 17%
Headache | 13% | 6% | 22% | 25%
Digestive System
Diarrhea | 23% | 18% | 23% | 32%
Dyspepsia | 4% | 5% | 8% | 12%
Nausea | 18% | 12% | 13% | 23%
Vomiting | 9% | 7% | 9% | 12%
Musculoskeletal
Arthralgia | 3% | 4% | 5% | 6%
Myalgia | 4% | 4% | 6% | 3%
Nervous System
Abnormal dreams | 2% | <1% | 11% | 19%
Depressive disorders | 6% | 10% | 9% | 13%
Dizziness | 4% | 5% | 25% | 26%
Insomnia | 7% | 3% | 16% | 21%
Neuropathy/peripheral neuritis | 4% | 3% | 4% | 13%
Paresthesia | 5% | 7% | 6% | 12%
Respiratory
Increased cough | 14% | 11% | 14% | 8%
Rhinitis | 18% | 12% | 12% | 10%
Skin
Rash event [Rash event includes rash, pruritus, maculopapular rash, urticaria, vesiculobullous rash, pustular rash, and allergic reaction.] | 17% | 14% | 30% | 33%

Studies 301A and 303 - Laboratory Abnormalities:

Laboratory abnormalities in these studies occurred with similar frequency in the EMTRIVA and comparator groups. A summary of Grade 3 and 4 laboratory abnormalities is provided in Table 3 below.

Table 3 Treatment-Emergent Grade 3/4 Laboratory Abnormalities Reported in ≥1% of EMTRIVA-Treated Patients in Either Study 301A or 303
 | 303 |  | 301A
 | EMTRIVA + ZDV/d4T + NNRTI/PI (N=294) | Lamivudine + ZDV/d4T + NNRTI/PI (N=146) | EMTRIVA + Didanosine + Efavirenz (N=286) | Stavudine + Didanosine + Efavirenz (N=285)
Percentage with grade 3 or grade 4 laboratory abnormality | 31% | 28% | 34% | 38%
ALT (>5.0 × ULN [ULN = Upper limit of normal]) | 2% | 1% | 5% | 6%
AST (>5.0 × ULN) | 3% | <1% | 6% | 9%
Bilirubin (>2.5 × ULN) | 1% | 2% | <1% | <1%
Creatine kinase (>4.0 × ULN) | 11% | 14% | 12% | 11%
Neutrophils (<750 mm^3) | 5% | 3% | 5% | 7%
Pancreatic amylase (>2.0 × ULN) | 2% | 2% | <1% | 1%
Serum amylase (>2.0 × ULN) | 2% | 2% | 5% | 10%
Serum glucose <40 or >250 mg/dL) | 3% | 3% | 2% | 3%
Serum lipase (>2.0 × ULN) | <1% | <1% | 1% | 2%
Triglycerides (>750 mg/dL) | 10% | 8% | 9% | 6%

Study 934 - Treatment Emergent Adverse Reactions: In Study 934, 511 antiretroviral-naïve patients received either VIREAD + EMTRIVA administered in combination with efavirenz (N=257) or zidovudine/lamivudine administered in combination with efavirenz (N=254). Adverse reactions observed in this study were generally consistent with those seen in previous studies in treatment-experienced or treatment-naïve patients (Table 4).

Table 4 Selected Treatment-Emergent Adverse Reactions [Frequencies of adverse reactions are based on all treatment-emergent adverse events, regardless of relationship to study drug.] (Grades 2–4) Reported in ≥5% in Any Treatment Group in Study 934 (0–144 Weeks)
 | TDF [From Weeks 96 to 144 of the study, patients received TRUVADA with efavirenz in place of VIREAD + EMTRIVA with efavirenz.] + EMTRIVA + EFV | AZT/3TC + EFV
 | N=257 | N=254
Gastrointestinal Disorder
Diarrhea | 9% | 5%
Nausea | 9% | 7%
Vomiting | 2% | 5%
General Disorders and Administration Site Condition
Fatigue | 9% | 8%
Infections and Infestations
Sinusitis | 8% | 4%
Upper respiratory tract infections | 8% | 5%
Nasopharyngitis | 5% | 3%
Nervous System Disorders
Headache | 6% | 5%
Dizziness | 8% | 7%
Psychiatric Disorders
Depression | 9% | 7%
Insomnia | 5% | 7%
Skin and Subcutaneous Tissue Disorders
Rash event [Rash event includes rash, exfoliative rash, rash generalized, rash macular, rash maculo-papular, rash pruritic, and rash vesicular.] | 7% | 9%

Study 934 – Laboratory Abnormalities: Significant laboratory abnormalities observed in this study are shown in Table 5.

Table 5 Significant Laboratory Abnormalities Reported in ≥1% of Patients in Any Treatment Group in Study 934 (0–144 Weeks)
 | TDF [From Weeks 96 to 144 of the study, patients received TRUVADA with efavirenz in place of VIREAD + EMTRIVA with efavirenz.] + EMTRIVA + EFV | AZT/3TC + EFV
 | N=257 | N=254
Any ≥ Grade 3 Laboratory Abnormality | 30% | 26%
Fasting Cholesterol (>240 mg/dL) | 22% | 24%
Creatine Kinase (M: >990 U/L) (F: >845 U/L) | 9% | 7%
Serum Amylase (>175 U/L) | 8% | 4%
Alkaline Phosphatase (>550 U/L) | 1% | 0%
AST (M: >180 U/L) (F: >170 U/L) | 3% | 3%
ALT (M: >215 U/L) (F: >170 U/L) | 2% | 3%
Hemoglobin (<8.0 mg/dL) | 0% | 4%
Hyperglycemia (>250 mg/dL) | 2% | 1%
Hematuria (>75 RBC/HPF) | 3% | 2%
Glycosuria (3+) | <1% | 1%
Neutrophils (<750/mm^3) | 3% | 5%
Fasting Triglycerides (>750 mg/dL) | 4% | 2%

Pediatric Patients

Assessment of adverse reactions is based on data from Study 203, an open label, uncontrolled study of 116 HIV-1-infected pediatric patients who received emtricitabine through 48 weeks. The adverse reaction profile in pediatric patients was generally comparable to that observed in clinical studies of EMTRIVA in adult patients [See Adverse Reactions (6.1)]. Hyperpigmentation was more frequent in children. Additional adverse reactions identified from this study include anemia.

Selected treatment-emergent adverse events, regardless of causality, reported in patients during 48 weeks of treatment were the following: infection (44%), hyperpigmentation (32%), increased cough (28%), vomiting (23%), otitis media (23%), rash (21%), rhinitis (20%), diarrhea (20%), fever (18%), pneumonia (15%), gastroenteritis (11%), abdominal pain (10%), and anemia (7%). Treatment-emergent grade 3/4 laboratory abnormalities were experienced by 9% of pediatric patients, including amylase >2.0 × ULN (n=4), neutrophils <750/mm^3 (n=3), ALT >5 × ULN (n=2), elevated CPK (>4 × ULN) (n=2) and one patient each with elevated bilirubin (>3.0 × ULN), elevated GGT (>10 × ULN), elevated lipase (>2.5 × ULN), decreased hemoglobin (<7 g/dL), and decreased glucose (<40 mg/dL).

7 DRUG INTERACTIONS

The potential for drug interactions with EMTRIVA has been studied in combination with zidovudine, indinavir, stavudine, famciclovir, and tenofovir disoproxil fumarate. There were no clinically significant drug interactions for any of these drugs Drug interactions studies are described elsewhere in the labeling [See Clinical Pharmacology (12.3)]

8 USE IN SPECIFIC POPULATIONS

8.1 Pregnancy

TERATOGENIC EFFECTS

Pregnancy Category B

The incidence of fetal variations and malformations was not increased in embryofetal toxicity studies performed with emtricitabine in mice at exposures (AUC) approximately 60-fold higher and in rabbits at approximately 120-fold higher than human exposures at the recommended daily dose. There are, however, no adequate and well-controlled studies in pregnant women. Because animal reproduction studies are not always predictive of human response, EMTRIVA should be used during pregnancy only if clearly needed.

Antiretroviral Pregnancy Registry: To monitor fetal outcomes of pregnant women exposed to EMTRIVA, an Antiretroviral Pregnancy Registry has been established. Healthcare providers are encouraged to register patients by calling 1–800–258–4263.

8.3 Nursing Mothers

Nursing Mothers: The Centers for Disease Control and Prevention recommend that HIV-1-infected mothers not breast-feed their infants to avoid risking postnatal transmission of HIV-1. It is not known whether emtricitabine is excreted in human milk. Because of both the potential for HIV-1 transmission and the potential for serious adverse reactions in nursing infants, mothers should be instructed not to breast-feed if they are receiving EMTRIVA.

8.4 Pediatric Use

The safety and efficacy of emtricitabine in patients between 3 months and 21 years of age is supported by data from three open-label, non-randomized clinical studies in which emtricitabine was administered to 169 HIV-1 infected treatment-naive and experienced (defined as virologically suppressed on a lamivudine containing regimen for which emtricitabine was substituted for lamivudine) subjects [See Clinical Studies(14.3)].

The pharmacokinetics of emtricitabine were studied in 20 neonates born to HIV-1-positive mothers [See Clinical Studies (14.3)]. All neonates were HIV-1 negative at the end of the study; the efficacy of emtricitabine in preventing or treating HIV-1 could not be determined.

8.5 Geriatric Use

Clinical studies of EMTRIVA did not include sufficient numbers of subjects aged 65 years and over to determine whether they respond differently from younger subjects. In general, dose selection for the elderly patient should be cautious, keeping in mind the greater frequency of decreased hepatic, renal, or cardiac function, and of concomitant disease or other drug therapy.

8.6 Patients with Impaired Renal Function

It is recommended that the dose or dosing interval for EMTRIVA be modified in patients with creatinine clearance <50 mL/min or in patients who require dialysis [See Dosage and Administration (2.5)].

10 OVERDOSAGE

There is no known antidote for EMTRIVA. Limited clinical experience is available at doses higher than the therapeutic dose of EMTRIVA. In one clinical pharmacology study single doses of emtricitabine 1200 mg were administered to 11 patients. No severe adverse reactions were reported.

The effects of higher doses are not known. If overdose occurs the patient should be monitored for signs of toxicity, and standard supportive treatment applied as necessary.

Hemodialysis treatment removes approximately 30% of the emtricitabine dose over a 3-hour dialysis period starting within 1.5 hours of emtricitabine dosing (blood flow rate of 400 mL/min and a dialysate flow rate of 600 mL/min). It is not known whether emtricitabine can be removed by peritoneal dialysis.

11 DESCRIPTION

EMTRIVA is the brand name of emtricitabine, a synthetic nucleoside analog with activity against human immunodeficiency virus type 1 (HIV-1) reverse transcriptase.

The chemical name of emtricitabine is 5-fluoro-1-(2R,5S)-[2-(hydroxymethyl)-1,3-oxathiolan-5-yl]cytosine. Emtricitabine is the (-) enantiomer of a thio analog of cytidine, which differs from other cytidine analogs in that it has a fluorine in the 5-position.

It has a molecular formula of C8H10FN3O3S and a molecular weight of 247.24. It has the following structural formula:

Emtricitabine is a white to off-white powder with a solubility of approximately 112 mg/mL in water at 25 °C. The log P for emtricitabine is -0.43 and the pKa is 2.65.

EMTRIVA is available as capsules or as an oral solution.

EMTRIVA capsules are for oral administration. Each capsule contains 200 mg of emtricitabine and the inactive ingredients, crospovidone, magnesium stearate, microcrystalline cellulose, and povidone.

EMTRIVA oral solution is for oral administration. One milliliter (1 mL) of EMTRIVA oral solution contains 10 mg of emtricitabine in an aqueous solution with the following inactive ingredients: cotton candy flavor, FD&C yellow No. 6, edetate disodium, methylparaben, and propylparaben (added as preservatives), sodium phosphate (monobasic), propylene glycol, water, and xylitol (added as a sweetener). Sodium hydroxide and hydrochloric acid may be used to adjust pH.

12 CLINICAL PHARMACOLOGY

12.1 Mechanism of Action

Emtricitabine is an antiviral drug. [See Clinical Pharmacology (12.4)]

12.3 Pharmacokinetics

Adult Subjects

The pharmacokinetics of emtricitabine were evaluated in healthy volunteers and HIV-1-infected individuals. Emtricitabine pharmacokinetics are similar between these populations.

Figure 1 shows the mean steady-state plasma emtricitabine concentration-time profile in 20 HIV-1-infected subjects receiving EMTRIVA capsules.

Figure 1 Mean (± 95% CI) Steady-State Plasma Emtricitabine Concentrations in HIV-1-Infected Adults (N=20)

Absorption

Emtricitabine is rapidly and extensively absorbed following oral administration with peak plasma concentrations occurring at 1–2 hours post-dose. Following multiple dose oral administration of EMTRIVA capsules to 20 HIV-1-infected subjects, the (mean ± SD) steady-state plasma emtricitabine peak concentration (Cmax) was 1.8 ± 0.7 µg/mL and the area-under the plasma concentration-time curve over a 24-hour dosing interval (AUC) was 10.0 ± 3.1 µg∙hr/mL. The mean steady state plasma trough concentration at 24 hours post-dose was 0.09 µg/mL. The mean absolute bioavailability of EMTRIVA capsules was 93% while the mean absolute bioavailability of EMTRIVA oral solution was 75%. The relative bioavailability of EMTRIVA oral solution was approximately 80% of EMTRIVA capsules.

The multiple dose pharmacokinetics of emtricitabine are dose proportional over a dose range of 25–200 mg.

Distribution

In vitro binding of emtricitabine to human plasma proteins was <4% and independent of concentration over the range of 0.02–200 µg/mL. At peak plasma concentration, the mean plasma to blood drug concentration ratio was ~1.0 and the mean semen to plasma drug concentration ratio was ~4.0.

Metabolism

In vitro studies indicate that emtricitabine is not an inhibitor of human CYP450 enzymes. Following administration of ^14C-emtricitabine, complete recovery of the dose was achieved in urine (~86%) and feces (~14%). Thirteen percent (13%) of the dose was recovered in urine as three putative metabolites. The biotransformation of emtricitabine includes oxidation of the thiol moiety to form the 3'-sulfoxide diastereomers (~9% of dose) and conjugation with glucuronic acid to form 2'-O-glucuronide (~4% of dose). No other metabolites were identifiable.

Elimination

The plasma emtricitabine half-life is approximately 10 hours. The renal clearance of emtricitabine is greater than the estimated creatinine clearance, suggesting elimination by both glomerular filtration and active tubular secretion. There may be competition for elimination with other compounds that are also renally eliminated.

Effects of Food on Oral Absorption

EMTRIVA capsules and oral solution may be taken with or without food. Emtricitabine systemic exposure (AUC) was unaffected while Cmax decreased by 29% when EMTRIVA capsules were administered with food (an approximately 1000 kcal high-fat meal). Emtricitabine systemic exposure (AUC) and Cmax were unaffected when 200 mg EMTRIVA oral solution was administered with either a high-fat or low-fat meal.

Special Populations

Race, Gender

The pharmacokinetics of emtricitabine were similar in adult male and female patients and no pharmacokinetic differences due to race have been identified.

Pediatric Patients

The pharmacokinetics of emtricitabine at steady state were determined in 77 HIV-1-infected children, and the pharmacokinetic profile was characterized in four age groups (Table 6). The emtricitabine exposure achieved in children receiving a daily dose of 6 mg/kg up to a maximum of 240 mg oral solution or a 200 mg capsule is similar to exposures achieved in adults receiving a once-daily dose of 200 mg.

The pharmacokinetics of emtricitabine were studied in 20 neonates born to HIV-1-positive mothers. Each mother received prenatal and intrapartum combination antiretroviral therapy. Neonates received up to 6 weeks of zidovudine prophylactically after birth. The neonates were administered two short courses of emtricitabine oral solution (each 3 mg/kg once daily × 4 days) during the first 3 months of life. The AUC observed in neonates who received a daily dose of 3 mg/kg of emtricitabine was similar to the AUC observed in pediatric patients ≥3 months to 17 years who received a daily dose of emtricitabine as a 6 mg/kg oral solution up to 240 mg or as a 200 mg capsule (Table 6).

Table 6 Mean ± SD Pharmacokinetic Parameters by Age Groups for Pediatric Patients and Neonates Receiving EMTRIVA Capsules or Oral Solution
 | HIV-1-exposed Neonates | HIV-1-infected Pediatric Patients
Age | 0–3 mo (N=20) [Two pharmacokinetic evaluations were conducted in 20 neonates over the first 3 months of life. Median (range) age of infant on day of pharmacokinetic evaluation was 26 (5–81) days.] | 3–24 mo (N=14) | 25 mo–6 yr (N=19) | 7–12yr (N=17) | 13–17 yr (N=27)
Formulation
Capsule (n) | 0 | 0 | 0 | 10 | 26
Oral Solution (n) | 20 | 14 | 19 | 7 | 1
Dose (mg/kg) [Mean (range)] | 3.1 (2.9–3.4) | 6.1 (5.5–6.8) | 6.1 (5.6–6.7) | 5.6 (3.1–6.6) | 4.4 (1.8–7.0)
Cmax (µg/mL) | 1.6 ± 0.6 | 1.9 ± 0.6 | 1.9 ± 0.7 | 2.7 ± 0.8 | 2.7 ± 0.9
AUC (µg∙hr/mL) | 11.0 ± 4.2 | 8.7 ± 3.2 | 9.0 ± 3.0 | 12.6 ± 3.5 | 12.6 ± 5.4
T1/2 (hr) | 12.1 ± 3.1 | 8.9 ± 3.2 | 11.3 ± 6.4 | 8.2 ± 3.2 | 8.9 ± 3.3

Geriatric Patients

The pharmacokinetics of emtricitabine have not been fully evaluated in the elderly.

Patients with Impaired Renal Function

The pharmacokinetics of emtricitabine are altered in patients with renal impairment [See Warnings and Precautions (5.4)]. In adult patients with creatinine clearance <50 mL/min or with end-stage renal disease (ESRD) requiring dialysis, Cmax and AUC of emtricitabine were increased due to a reduction in renal clearance (Table 7). It is recommended that the dosing interval for EMTRIVA be modified in adult patients with creatinine clearance <50 mL/min or in adult patients with ESRD who require dialysis [See Dosage and Administration (2.5)]. The effects of renal impairment on emtricitabine pharmacokinetics in pediatric patients are not known.

Table 7 Mean ± SD Pharmacokinetic Parameters in Adult Patients with Varying Degrees of Renal Function
Creatinine Clearance (mL/min) | >80 (N=6) | 50–80 (N=6) | 30–49 (N=6) | <30 (N=5) | ESRD [ESRD patients requiring dialysis] <30 (N=5)
Baseline creatinine clearance (mL/min) | 107 ± 21 | 59.8 ± 6.5 | 40.9 ± 5.1 | 22.9 ± 5.3 | 8.8 ± 1.4
Cmax (µg/mL) | 2.2 ± 0.6 | 3.8 ± 0.9 | 3.2 ± 0.6 | 2.8 ± 0.7 | 2.8 ± 0.5
AUC (µg∙hr/mL) | 11.8 ± 2.9 | 19.9 ± 1.2 | 25.1 ± 5.7 | 33.7± 2.1 | 53.2 ± 9.9
CL/F (mL/min) | 302 ± 94 | 168 ± 10 | 138 ± 28 | 99 ± 6 | 64 ± 12
CLr (mL/min) | 213 ± 89 | 121 ± 39 | 69 ± 32 | 30 ± 11 | NA [NA = Not Applicable]

Hemodialysis: Hemodialysis treatment removes approximately 30% of the emtricitabine dose over a 3-hour dialysis period starting within 1.5 hours of emtricitabine dosing (blood flow rate of 400 mL/min and a dialysate flow rate of 600 mL/min). It is not known whether emtricitabine can be removed by peritoneal dialysis.

Patients with Hepatic Impairment

The pharmacokinetics of emtricitabine have not been studied in patients with hepatic impairment, however, emtricitabine is not metabolized by liver enzymes, so the impact of liver impairment should be limited.

Assessment of Drug Interactions

At concentrations up to 14-fold higher than those observed in vivo, emtricitabine did not inhibit in vitro drug metabolism mediated by any of the following human CYP isoforms: CYP1A2, CYP2A6, CYP2B6, CYP2C9, CYP2C19, CYP2D6, and CYP3A4. Emtricitabine did not inhibit the enzyme responsible for glucuronidation (uridine-5'-disphosphoglucuronyl transferase). Based on the results of these in vitro experiments and the known elimination pathways of emtricitabine, the potential for CYP mediated interactions involving emtricitabine with other medicinal products is low.

EMTRIVA has been evaluated in healthy volunteers in combination with tenofovir disoproxil fumarate (DF), zidovudine, indinavir, famciclovir, and stavudine. Tables 8 and 9 summarize the pharmacokinetic effects of coadministered drug on emtricitabine pharmacokinetics and effects of emtricitabine on the pharmacokinetics of coadministered drug.

Table 8 Drug Interactions: Change in Pharmacokinetic Parameters for Emtricitabine in the Presence of the Coadministered Drug [All interaction studies conducted in healthy volunteers.]
Coadministered Drug | Dose of Coadministered Drug (mg) | Emtricitabine Dose (mg) | N | % Change of Emtricitabine Pharmacokinetic Parameters [↑ = Increase; ↓ = Decrease; = No Effect; NA = Not Applicable] (90% CI)
Coadministered Drug | Dose of Coadministered Drug (mg) | Emtricitabine Dose (mg) | N | Cmax | AUC | Cmin
Tenofovir DF | 300 once daily x 7 days | 200 once daily × 7 days | 17 |  |  | ↑ 20 (↑ 12 to ↑ 29)
Zidovudine | 300 twice daily × 7 days | 200 once daily × 7 days | 27
Indinavir | 800 × 1 | 200 × 1 | 12 |  |  | NA
Famciclovir | 500 × 1 | 200 × 1 | 12 |  |  | NA
Stavudine | 40 × 1 | 200 × 1 | 6 |  |  | NA

Table 9 Drug Interactions: Change in Pharmacokinetic Parameters for Coadministered Drug in the Presence of Emtricitabine [All interaction studies conducted in healthy volunteers.]
Coadministered Drug | Dose of Coadministered Drug (mg) | Emtricitabine Dose (mg) | N | % Change of Coadministered Drug Pharmacokinetic Parameters [↑ = Increase; ↓ = Decrease; = No Effect; NA = Not Applicable] (90% CI)
Coadministered Drug | Dose of Coadministered Drug (mg) | Emtricitabine Dose (mg) | N | Cmax | AUC | Cmin
Tenofovir DF | 300 once daily × 7 days | 200 once daily × 7 days | 17
Zidovudine | 300 twice daily × 7 days | 200 once daily × 7 days | 27 | ↑ 17 (↑ 0 to ↑ 38) | ↑ 13 (↑ 5 to↑ 20)
Indinavir | 800 × 1 | 200 × 1 | 12 |  |  | NA
Famciclovir | 500 × 1 | 200 × 1 | 12 |  |  | NA
Stavudine | 40 × 1 | 200 × 1 | 6 |  |  | NA

12.4 Microbiology

Mechanism of Action

Emtricitabine, a synthetic nucleoside analog of cytidine, is phosphorylated by cellular enzymes to form emtricitabine 5'-triphosphate. Emtricitabine 5'-triphosphate inhibits the activity of the HIV-1 reverse transcriptase by competing with the natural substrate deoxycytidine 5'-triphosphate and by being incorporated into nascent viral DNA which results in chain termination. Emtricitabine 5'-triphosphate is a weak inhibitor of mammalian DNA polymerase α, β, ε, and mitochondrial DNA polymerase γ.

Antiviral Activity

The antiviral activity in cell culture of emtricitabine against laboratory and clinical isolates of HIV-1 was assessed in lymphoblastoid cell lines, the MAGI-CCR5 cell line, and peripheral blood mononuclear cells. The 50% effective concentration (EC50) value for emtricitabine was in the range of 0.0013–0.64 µM (0.0003–0.158 µg/mL). In drug combination studies of emtricitabine with nucleoside reverse transcriptase inhibitors (abacavir, lamivudine, stavudine, tenofovir, zalcitabine, zidovudine), non-nucleoside reverse transcriptase inhibitors (delavirdine, efavirenz, nevirapine), and protease inhibitors (amprenavir, nelfinavir, ritonavir, saquinavir), additive to synergistic effects were observed. Emtricitabine displayed antiviral activity in cell culture against HIV-1 clades A, B, C, D, E, F, and G (EC50 values ranged from 0.007–0.075 µM) and showed strain specific activity against HIV-2 (EC50 values ranged from 0.007–1.5 µM).

The in vivo activity of emtricitabine was evaluated in two clinical trials in which 101 patients were administered 25–400 mg a day of EMTRIVA as monotherapy for 10–14 days. A dose-related antiviral effect was observed, with a median decrease from baseline in plasma HIV-1 RNA of 1.3 log10 at a dose of 25 mg once daily and 1.7 log10 to 1.9 log10 at a dose of 200 mg once daily or twice daily.

Resistance

Emtricitabine-resistant isolates of HIV-1 have been selected in cell culture and in vivo. Genotypic analysis of these isolates showed that the reduced susceptibility to emtricitabine was associated with a substitution in the HIV-1 reverse transcriptase gene at codon 184 which resulted in an amino acid substitution of methionine by valine or isoleucine (M184V/I).

Emtricitabine-resistant isolates of HIV-1 have been recovered from some patients treated with emtricitabine alone or in combination with other antiretroviral agents. In a clinical study of treatment-naive patients treated with EMTRIVA, didanosine, and efavirenz [See Clinical Studies (14.1)], viral isolates from 37.5% of patients with virologic failure showed reduced susceptibility to emtricitabine. Genotypic analysis of these isolates showed that the resistance was due to M184V/I substitutions in the HIV-1 reverse transcriptase gene.

In a clinical study of treatment-naive patients treated with either EMTRIVA, VIREAD, and efavirenz or zidovudine/lamivudine and efavirenz [See Clinical Studies (14.1)], resistance analysis was performed on HIV-1 isolates from all confirmed virologic failure patients with >400 copies/mL of HIV-1 RNA at Week 144 or early discontinuation. Development of efavirenz resistance-associated substitutions occurred most frequently and was similar between the treatment arms. The M184V amino acid substitution, associated with resistance to EMTRIVA and lamivudine, was observed in 2/19 analyzed patient isolates in the EMTRIVA + VIREAD group and in 10/29 analyzed patient isolates in the lamivudine/zidovudine group. Through 144 weeks of Study 934, no patients have developed a detectable K65R substitution in their HIV-1 as analyzed through standard genotypic analysis.

Cross Resistance

Cross-resistance among certain nucleoside analog reverse transcriptase inhibitors has been recognized. Emtricitabine-resistant isolates (M184V/I) were cross-resistant to lamivudine and zalcitabine but retained sensitivity in cell culture to didanosine, stavudine, tenofovir, zidovudine, and NNRTIs (delavirdine, efavirenz, and nevirapine). HIV-1 isolates containing the K65R substitution, selected in vivo by abacavir, didanosine, tenofovir, and zalcitabine, demonstrated reduced susceptibility to inhibition by emtricitabine. Viruses harboring substitutions conferring reduced susceptibility to stavudine and zidovudine (M41L, D67N, K70R, L210W, T215Y/F, K219Q/E) or didanosine (L74V) remained sensitive to emtricitabine. HIV-1 containing the K103N substitution associated with resistance to NNRTIs was susceptible to emtricitabine.

13 NONCLINICAL TOXICOLOGY

13.1 Carcinogenesis, Mutagenesis, Impairment of Fertility

In long-term oral carcinogenicity studies of emtricitabine, no drug-related increases in tumor incidence were found in mice at doses up to 750 mg/kg/day (26 times the human systemic exposure at the therapeutic dose of 200 mg/day) or in rats at doses up to 600 mg/kg/day (31 times the human systemic exposure at the therapeutic dose).

Emtricitabine was not genotoxic in the reverse mutation bacterial test (Ames test), mouse lymphoma or mouse micronucleus assays.

Emtricitabine did not affect fertility in male rats at approximately 140-fold or in male and female mice at approximately 60-fold higher exposures (AUC) than in humans given the recommended 200 mg daily dose. Fertility was normal in the offspring of mice exposed daily from before birth (in utero) through sexual maturity at daily exposures (AUC) of approximately 60-fold higher than human exposures at the recommended 200 mg daily dose.

14 CLINICAL STUDIES

14.1 Treatment-Naive Adult Patients

Study 934

Data through 144 weeks are reported for Study 934, a randomized, open-label, active-controlled multicenter study comparing EMTRIVA + VIREAD administered in combination with efavirenz versus zidovudine/lamivudine fixed-dose combination administered in combination with efavirenz in 511 antiretroviral-naive patients. From Weeks 96 to 144 of the study, patients received emtricitabine + tenofovir disoproxil fumarate (tenofovir DF) with efavirenz in place of EMTRIVA + tenofovir DF with efavirenz. Patients had a mean age of 38 years (range 18–80), 86% were male, 59% were Caucasian and 23% were Black. The mean baseline CD4^+ cell count was 245 cells/mm^3 (range 2–1191) and median baseline plasma HIV-1 RNA was 5.01 log10 copies/mL (range 3.56–6.54). Patients were stratified by baseline CD4^+ cell count (< or ≥200 cells/mm^3); 41% had CD4^+ cell counts <200 cells/mm^3 and 51% of patients had baseline viral loads >100,000 copies/mL. Treatment outcomes through 48 and 144 weeks for those patients who did not have efavirenz resistance at baseline are presented in Table 10.

Table 10 Outcomes of Randomized Treatment at Week 48 and 144 (Study 934)
Outcomes | Week 48 |  | Week 144
Outcomes | EMTRIVA +TDF +EFV (N=244) | AZT/3TC +EFV (N=243) | EMTRIVA +TDF +EFV (N=227) [Patients who were responders at Week 48 or Week 96 (HIV-1 RNA <400 copies/mL) but did not consent to continue study after Week 48 or Week 96 were excluded from analysis.] | AZT/3TC +EFV (N=229)
Responder [Patients achieved and maintained confirmed HIV-1 RNA <400 copies/mL through Weeks 48 and 144.] | 84% | 73% | 71% | 58%
Virologic failure [Includes confirmed viral rebound and failure to achieve confirmed <400 copies/mL through Weeks 48 and 144.] | 2% | 4% | 3% | 6%
Rebound | 1% | 3% | 2% | 5%
Never suppressed | 0% | 0% | 0% | 0%
Change in antiretroviral regimen | 1% | 1% | 1% | 1%
Death | <1% | 1% | 1% | 1%
Discontinued due to adverse event | 4% | 9% | 5% | 12%
Discontinued for other reasons [Includes lost to follow-up, patient withdrawal, noncompliance, protocol violation and other reasons.] | 10% | 14% | 20% | 22%

Through Week 48, 84% and 73% of patients in the EMTRIVA + tenofovir DF group and the zidovudine/lamivudine group, respectively, achieved and maintained HIV-1 RNA <400 copies/mL (71% and 58% through Week 144). The difference in the proportion of patients who achieved and maintained HIV-1 RNA <400 copies/mL through 48 weeks largely results from the higher number of discontinuations due to adverse events and other reasons in the zidovudine/lamivudine group in this open-label study. In addition, 80% and 70% of patients in the EMTRIVA + tenofovir DF group and the zidovudine/lamivudine group, respectively, achieved and maintained HIV-1 RNA <50 copies/mL through Week 48 (64% and 56% through Week 144). The mean increase from baseline in CD4^+ cell count was 190 cells/mm^3 in the EMTRIVA + tenofovir DF group and 158 cells/mm^3 in the zidovudine/lamivudine group at Week 48 (312 and 271 cells/mm^3 at Week 144).

Through 48 weeks, 7 patients in the EMTRIVA + tenofovir DF group and 5 patients in the zidovudine/lamivudine group experienced a new CDC Class C event (10 and 6 patients through 144 weeks).

Study 301A

Study 301A was a 48 week double-blind, active-controlled multicenter study comparing EMTRIVA (200 mg once daily) administered in combination with didanosine and efavirenz versus stavudine, didanosine and efavirenz in 571 antiretroviral naive adult patients. Patients had a mean age of 36 years (range 18–69), 85% were male, 52% Caucasian, 16% African-American and 26% Hispanic. Patients had a mean baseline CD4^+ cell count of 318 cells/mm^3 (range 5–1317) and a median baseline plasma HIV-1 RNA of 4.9 log10 copies/mL (range 2.6–7.0). Thirty-eight percent of patients had baseline viral loads >100,000 copies/mL and 31% had CD4^+ cell counts <200 cells/mL. Treatment outcomes are presented in Table 11 below.

Table 11 Outcomes of Randomized Treatment at Week 48 (Study 301A)
Outcomes | EMTRIVA + Didanosine + Efavirenz (N=286) | Stavudine + Didanosine + Efavirenz (N=285)
Responder [Patients achieved and maintained confirmed HIV RNA <400 copies/mL (<50 copies/mL) through Week 48.] | 81% (78%) | 68% (59%)
Virologic Failure [Includes patients who failed to achieve virologic suppression or rebounded after achieving virologic suppression.] | 3% | 11%
Death | 0% | <1%
Study Discontinuation Due to Adverse Event | 7% | 13%
Study Discontinuation for Other Reasons [Includes lost to follow-up, patient withdrawal, non-compliance, protocol violation and other reasons.] | 9% | 8%

The mean increase from baseline in CD4^+ cell count was 168 cells/mm^3 for the EMTRIVA arm and 134 cells/mm^3 for the stavudine arm.

Through 48 weeks in the EMTRIVA group, 5 patients (1.7%) experienced a new CDC Class C event, compared to 7 patients (2.5%) in the stavudine group.

14.2 Treatment-Experienced Adult Patients

Study 303

Study 303 was a 48 week, open-label, active-controlled multicenter study comparing EMTRIVA (200 mg once daily) to lamivudine, in combination with stavudine or zidovudine and a protease inhibitor or NNRTI in 440 adult patients who were on a lamivudine-containing triple-antiretroviral drug regimen for at least 12 weeks prior to study entry and had HIV-1 RNA ≤400 copies/mL.

Patients were randomized 1:2 to continue therapy with lamivudine (150 mg twice daily) or to switch to EMTRIVA (200 mg once daily). All patients were maintained on their stable background regimen. Patients had a mean age of 42 years (range 22–80), 86% were male, 64% Caucasian, 21% African-American and 13% Hispanic. Patients had a mean baseline CD4^+ cell count of 527 cells/mm^3 (range 37–1909), and a median baseline plasma HIV-1 RNA of 1.7 log10 copies/mL (range 1.7–4.0).

The median duration of prior antiretroviral therapy was 27.6 months. Treatment outcomes are presented in Table 12 below.

Table 12 Outcomes of Randomized Treatment at Week 48 (Study 303)
Outcomes | EMTRIVA + ZDV/d4T + NNRTI/PI (N=294) | Lamivudine + ZDV/d4T + NNRTI/PI (N=146)
Responder [Patients achieved and maintained confirmed HIV RNA <400 copies/mL (<50 copies/mL) through Week 48.] | 77% (67%) | 82% (72%)
Virologic Failure [Includes patients who failed to achieve virologic suppression or rebounded after achieving virologic suppression.] | 7% | 8%
Death | 0% | <1%
Study Discontinuation Due to Adverse Event | 4% | 0%
Study Discontinuation for Other Reasons [Includes lost to follow-up, patient withdrawal, non-compliance, protocol violation and other reasons.] | 12% | 10%

The mean increase from baseline in CD4^+ cell count was 29 cells/mm^3 for the EMTRIVA arm and 61 cells/mm^3 for the lamivudine arm.

Through 48 weeks, in the EMTRIVA group 2 patients (0.7%) experienced a new CDC Class C event, compared to 2 patients (1.4%) in the lamivudine group.

14.3 Pediatric Patients

In three open-label, non-randomized clinical studies, emtricitabine was administered to 169 HIV-1 infected treatment-naive and experienced (defined as virologically suppressed on a lamivudine containing regimen for which emtricitabine was substituted for lamivudine) patients between 3 months and 21 years of age. Patients received once-daily EMTRIVA oral solution (6 mg/kg to a maximum of 240 mg/day) or EMTRIVA capsules (a single 200 mg capsule once daily) in combination with at least two other antiretroviral agents.

Patients had a mean age of 7.9 years (range 0.3–21), 49% were male, 15% Caucasian, 61% Black and 24% Hispanic. Patients had a median baseline HIV-1 RNA of 4.6 log10 copies/mL (range 1.7–6.4) and a mean baseline CD4^+ cell count of 745 cells/mm^3 (range 2–2650). Through 48 weeks of therapy, the overall proportion of patients who achieved and sustained an HIV-1 RNA <400 copies/mL was 86%, and <50 copies/mL was 73%. The mean increase from baseline in CD4^+ cell count was 232 cells/mm^3 (-945, +1512). The adverse reaction profile observed during these clinical trials was similar to that of adult patients, with the exception of the occurrence of anemia and higher frequency of hyperpigmentation in children [See Adverse Reactions (6)].

The pharmacokinetics of emtricitabine were studied in 20 neonates born to HIV-1-positive mothers. Each mother received prenatal and intrapartum combination antiretroviral therapy. Neonates received up to 6 weeks of zidovudine prophylactically after birth. The neonates were administered two short courses of emtricitabine oral solution (each 3 mg/kg once daily × 4 days) during the first 3 months of life. Emtricitabine exposures in neonates were similar to the exposures achieved in patients >3 months to 17 years [See Clinical Pharmacology (12.3)]. During the two short dosing periods on emtricitabine there were no safety issues identified in the treated neonates. All neonates were HIV-1 negative at the end of the study; the efficacy of emtricitabine in preventing or treating HIV-1 could not be determined.

16 HOW SUPPLIED/STORAGE AND HANDLING

Capsules

The size 1 hard gelatin capsules with a blue cap and white body contain 200 mg of emtricitabine, are printed with "200 mg" in black on the cap and "GILEAD" and the corporate logo in black on the body, and are available in unit of use bottles (closed with induction sealed child-resistant closures) of:

- 30 capsules (NDC 61958–0601–1).

STORAGE AND HANDLING

Store at 25 °C (77 °F); excursions permitted to 15 °C–30 °C (59 °F–86 °F)

Oral Solution

The oral solution is a clear, orange to dark orange liquid, contains 10 mg/mL of emtricitabine, and is available in unit of use plastic, amber bottles (closed with child resistant closures and packaged with a marked dosing cup) of:

- 170 mL (NDC 61958–0602–1).

STORAGE AND HANDLING

Store refrigerated, 2–8 °C (36–46 °F). Emtriva oral solution should be used within 3 months if stored by the patient at 25 °C (77 °F); excursions permitted to 15–30 °C (59–86 °F).

17 PATIENT COUNSELING INFORMATION

See FDA-approved patient labeling (17.2)

17.1 Information for Patients

Patients should be advised that:

- EMTRIVA is not a cure for HIV-1 infection and patients may continue to experience illnesses associated with HIV-1 infection, including opportunistic infections. Patients should remain under the care of a physician when using EMTRIVA.
- The use of EMTRIVA has not been shown to reduce the risk of transmission of HIV-1 to others through sexual contact or blood contamination.
- The long term effects of EMTRIVA are unknown.
- EMTRIVA capsules and oral solution are for oral ingestion only.
- It is important to take EMTRIVA with combination therapy on a regular dosing schedule to avoid missing doses.
- Lactic acidosis and severe hepatomegaly with steatosis, including fatal cases, have been reported. Treatment with EMTRIVA should be suspended in any patient who develops clinical symptoms suggestive of lactic acidosis or pronounced hepatotoxicity (including nausea, vomiting, unusual or unexpected stomach discomfort, and weakness) [See Warnings and Precautions (5.1)].
- Patients with HIV-1 should be tested for Hepatitis B virus (HBV) before initiating antiretroviral therapy.
- Severe acute exacerbations of Hepatitis B have been reported in patients who are coinfected with HBV and HIV-1 and have discontinued EMTRIVA.
- EMTRIVA should not be coadministered with ATRIPLA, COMPLERA, or TRUVADA; or with other drugs containing lamivudine, including Combivir (lamivudine/zidovudine), Epivir or Epivir-HBV (lamivudine), Epzicom (abacavir sulfate/lamivudine), or Trizivir (abacavir sulfate/lamivudine/zidovudine) [See Warnings and Precautions (5.3)].
- Dose or dosing interval of EMTRIVA may need adjustment in patients with renal impairment [See Dosage and Administration (2.5)].

PATIENT INFORMATION

EMTRIVA® (em-treev'-ah) capsules

EMTRIVA oral solution

Generic name: emtricitabine (em tri SIT uh bean)

Read the Patient Information that comes with EMTRIVA before you start using it and each time you get a refill. There may be new information. This information does not take the place of talking to your healthcare provider about your medical condition or treatment.

You should stay under a healthcare provider's care when taking EMTRIVA. Do not change or stop your medicine without first talking with your healthcare provider. Talk to your healthcare provider or pharmacist if you have any questions about EMTRIVA.

What is the most important information I should know about EMTRIVA?

- Some people who have taken medicines like EMTRIVA (a nucleoside analog) have developed a serious condition called lactic acidosis (buildup of an acid in the blood). Lactic acidosis can be a medical emergency and may need to be treated in the hospital. Call your healthcare provider right away if you get the following signs of lactic acidosis.
  - You feel very weak or tired.
  - You have unusual (not normal) muscle pain.
  - You have trouble breathing.
  - You have stomach pain with nausea and vomiting.
  - You feel cold, especially in your arm and legs.
  - You feel dizzy or lightheaded.
  - You have a fast or irregular heartbeat.
- Some people who have taken medicines like EMTRIVA have developed serious liver problems called hepatotoxicity, with liver enlargement (hepatomegaly) and fat in the liver (steatosis). Call your healthcare provider right away if you get the following signs of liver problems.
  - Your skin or the white part of your eyes turns yellow (jaundice).
  - Your urine turns dark.
  - Your bowel movements (stools) turn light in color.
  - You don't feel like eating food for several days or longer.
  - You feel sick to your stomach (nausea).
  - You have lower stomach area (abdominal) pain.
- You may be more likely to get lactic acidosis or liver problems if you are female, very overweight (obese), or have been taking nucleoside analog medicines, like EMTRIVA, for a long time.
- If you are also infected with the Hepatitis B Virus (HBV), you need close medical follow-up for several months after stopping treatment with EMTRIVA. Follow-up includes medical exams and blood tests to check for HBV that is getting worse. Patients with HBV infection, who take EMTRIVA and then stop it, may get "flare-ups" of their hepatitis. A "flare-up" is when the disease suddenly returns in a worse way than before.

What is EMTRIVA?

EMTRIVA is a type of medicine called an HIV-1 (human immunodeficiency virus) nucleoside reverse transcriptase inhibitor (NRTI). EMTRIVA is always used with other anti-HIV-1 medicines to treat people with HIV-1 infection. EMTRIVA is for adults and children, but has not been studied fully in adults over age 65.

HIV infection destroys CD4^+ T cells, which are important to the immune system. The immune system helps fight infection. After a large number of T cells are destroyed, acquired immune deficiency syndrome (AIDS) develops.

EMTRIVA helps to block HIV-1 reverse transcriptase, a chemical in your body (enzyme) that is needed for HIV-1 to multiply. EMTRIVA may lower the amount of HIV-1 in the blood (viral load). EMTRIVA may also help to increase the number of T cells called CD4^+ cells. Lowering the amount of HIV-1 in the blood lowers the chance of death or infections that happen when your immune system is weak (opportunistic infections).

EMTRIVA does not cure HIV-1 infection or AIDS. The long-term effects of EMTRIVA are not known at this time. People taking EMTRIVA may still get opportunistic infections or other conditions that happen with HIV-1 infection. Opportunistic infections are infections that develop because the immune system is weak. Some of these conditions are pneumonia, herpes virus infections, and Mycobacterium avium complex (MAC) infections. It is very important that you see your healthcare provider regularly while taking EMTRIVA.

EMTRIVA does not lower your chance of passing HIV-1 to other people through sexual contact, sharing needles, or being exposed to your blood. For your health and the health of others, it is important to always practice safer sex by using a latex or polyurethane condom or other barrier to lower the chance of sexual contact with semen, vaginal secretions, or blood. Never use or share dirty needles.

Who should not take EMTRIVA?

- Do not take EMTRIVA if you are allergic to EMTRIVA or any of its ingredients. The active ingredient is emtricitabine. See the end of this leaflet for a complete list of ingredients.
- Do not take EMTRIVA if you are already taking ATRIPLA®, COMPLERA™, TRUVADA®, Combivir, Epivir, Epivir-HBV, Epzicom, or Trizivir because these medicines contain the same or similar active ingredients.

What should I tell my healthcare provider before taking EMTRIVA?

Tell your healthcare provider

- If you are pregnant or planning to become pregnant. We do not know if EMTRIVA can harm your unborn child. You and your healthcare provider will need to decide if EMTRIVA is right for you. If you use EMTRIVA while you are pregnant, talk to your healthcare provider about how you can be on the EMTRIVA Antiviral Pregnancy Registry.
- If you are breast-feeding. You should not breast feed if you are HIV-positive because of the chance of passing the HIV virus to your baby. Also, it is not known if EMTRIVA can pass into your breast milk and if it can harm your baby. If you are a woman who has or will have a baby, talk with your healthcare provider about the best way to feed your baby.
- If you have kidney problems. You may need to take EMTRIVA less often.
- If you have any liver problems including Hepatitis B Virus infection.
- Tell your healthcare provider about all your medical conditions.
- Tell your healthcare provider about all the medicines you take such as prescription and non-prescription medicines and dietary supplements. Keep a complete list of all the medicines that you take. Make a new list when medicines are added or stopped. Give copies of this list to all of your healthcare providers and pharmacist every time you visit or fill a prescription.

How should I take EMTRIVA?

- Take EMTRIVA by mouth exactly as your healthcare provider prescribed it. Follow the directions from your healthcare provider, exactly as written on the label.
- Dosing in adults: The usual dose of EMTRIVA is 1 capsule once a day.
- Dosing in children: The child's doctor will calculate the right dose of EMTRIVA (oral solution or capsule) based on the child's weight.
- EMTRIVA is always used with other anti-HIV-1 medicines.
- EMTRIVA may be taken with or without a meal. Food does not affect how EMTRIVA works.
- If you forget to take EMTRIVA, take it as soon as you remember that day. Do not take more than 1 dose of EMTRIVA in a day. Do not take 2 doses at the same time. Call your healthcare provider or pharmacist if you are not sure what to do. It is important that you do not miss any doses of EMTRIVA or your other anti-HIV-1 medicines.
- When your EMTRIVA supply starts to run low, get more from your healthcare provider or pharmacy. This is very important because the amount of virus in your blood may increase if the medicine is stopped for even a short time. The virus may develop resistance to EMTRIVA and become harder to treat.
- Stay under a healthcare provider's care when taking EMTRIVA. Do not change your treatment or stop treatment without first talking with your healthcare provider.
- If you take too much EMTRIVA, call your local poison control center or emergency room right away.

What should I avoid while taking EMTRIVA?

- Do not breast-feed. See "What should I tell my healthcare provider before taking EMTRIVA?" Talk with your healthcare provider about the best way to feed your baby.
- Avoid doing things that can spread HIV-1 infection since EMTRIVA doesn't stop you from passing the HIV-1 infection to others.
- Do not share needles or other injection equipment.
- Do not share personal items that can have blood or body fluids on them, like toothbrushes or razor blades.
- Do not have any kind of sex without protection. Always practice safer sex by using a latex or polyurethane condom or other barrier to reduce the chance of sexual contact with semen, vaginal secretions, or blood.

What are the possible side effects of EMTRIVA?

EMTRIVA may cause the following serious side effects (See "What is the most important information I should know about EMTRIVA?"):

- lactic acidosis (buildup of an acid in the blood). Lactic acidosis can be a medical emergency and may need to be treated in the hospital. Call your doctor right away if you get signs of lactic acidosis. (See "What is the most important information I should know about EMTRIVA?")
- serious liver problems (hepatotoxicity), with liver enlargement (hepatomegaly) and fat in the liver (steatosis). Call your healthcare provider right away if you get any signs of liver problems. (See "What is the most important information I should know about EMTRIVA?")
- "flare-ups" of Hepatitis B Virus infection, in which the disease suddenly returns in a worse way than before, can occur if you stop taking EMTRIVA. EMTRIVA is not for the treatment of Hepatitis B Virus (HBV) infection.

Other side effects with EMTRIVA when used with other anti-HIV-1 medicines Include:

- Changes in body fat have been seen in some patients taking EMTRIVA and other anti-HIV-1 medicines. These changes may include increased amount of fat in the upper back and neck ("buffalo hump"), breast, and around the main part of your body (trunk). Loss of fat from the legs, arms and face may also happen. The cause and long term health effects of these conditions are not known at this time.

The most common side effects of EMTRIVA used with other anti-HIV-1 medicines are headache, diarrhea, and nausea. Other side effects include allergic reaction, dizziness, sleeping problems, abnormal dreams, vomiting, indigestion, stomach pain, pain, weakness and rash. Skin discoloration may also happen with EMTRIVA.

There have been other side effects in patients taking EMTRIVA. However, these side effects may have been due to other medicines that patients were taking or to HIV-1 itself. Some of these side effects can be serious.

This list of side effects is not complete. If you have questions about side effects, ask your healthcare provider or pharmacist. You should report any new or continuing symptoms to your healthcare provider right away. Your healthcare provider may be able to help you manage these side effects.

How do I store EMTRIVA?

- Keep EMTRIVA and all other medicines out of reach of children.
- Store EMTRIVA capsules between 59 °F and 86 °F (15 °C to 30 °C).
- Store EMTRIVA oral solution in a refrigerator between 36 °F and 46 °F (2–8 °C). Do not freeze. Alternatively, the product may be stored at room temperature for up to 3 months and any remaining solution in the bottle must be discarded after the 3 months.
- Do not keep your medicine in places that are too hot or cold.
- Do not keep medicine that is out of date or that you no longer need. If you throw any medicines away make sure that children will not find them.

General information about EMTRIVA:

Medicines are sometimes prescribed for conditions that are not mentioned in patient information leaflets. Do not use EMTRIVA for a condition for which it was not prescribed. Do not give EMTRIVA to other people, even if they have the same symptoms you have. It may harm them.

This leaflet summarizes the most important information about EMTRIVA. If you would like more information, talk with your doctor. You can ask your healthcare provider or pharmacist for information about EMTRIVA that is written for health professionals. For more information, you may also call 1-800-GILEAD5.

What are the ingredients of EMTRIVA?

Active Ingredient: emtricitabine

Inactive Ingredients for EMTRIVA capsules: crospovidone, magnesium stearate, microcrystalline cellulose, and povidone.

Inactive Ingredients for EMTRIVA oral solution: Cotton candy flavor, FD&C yellow No. 6, edetate disodium, methylparaben and propylparaben, sodium phosphate (monobasic), propylene glycol, water, and xylitol. Sodium hydroxide and hydrochloric acid may be used to adjust pH.

Rx Only

November 2011

COMPLERA, EMTRIVA, TRUVADA, and VIREAD are trademarks or registered trademarks of Gilead Sciences, Inc., or its related companies. ATRIPLA is a registered trademark of Bristol-Myers Squibb & Gilead Sciences, LLC. All other trademarks referenced herein are the property of their respective owners.

21-500-896-GS-015 18112011

Additional barcode labeling by:
Physicians Total Care, Inc.
Tulsa, Oklahoma 74146

PRINCIPAL DISPLAY PANEL - Representative Bottle Label

NDC 54868-4853-0

Emtriva®
(emtricitabine)
Capsules, 200 mg

30 capsules

Rx only